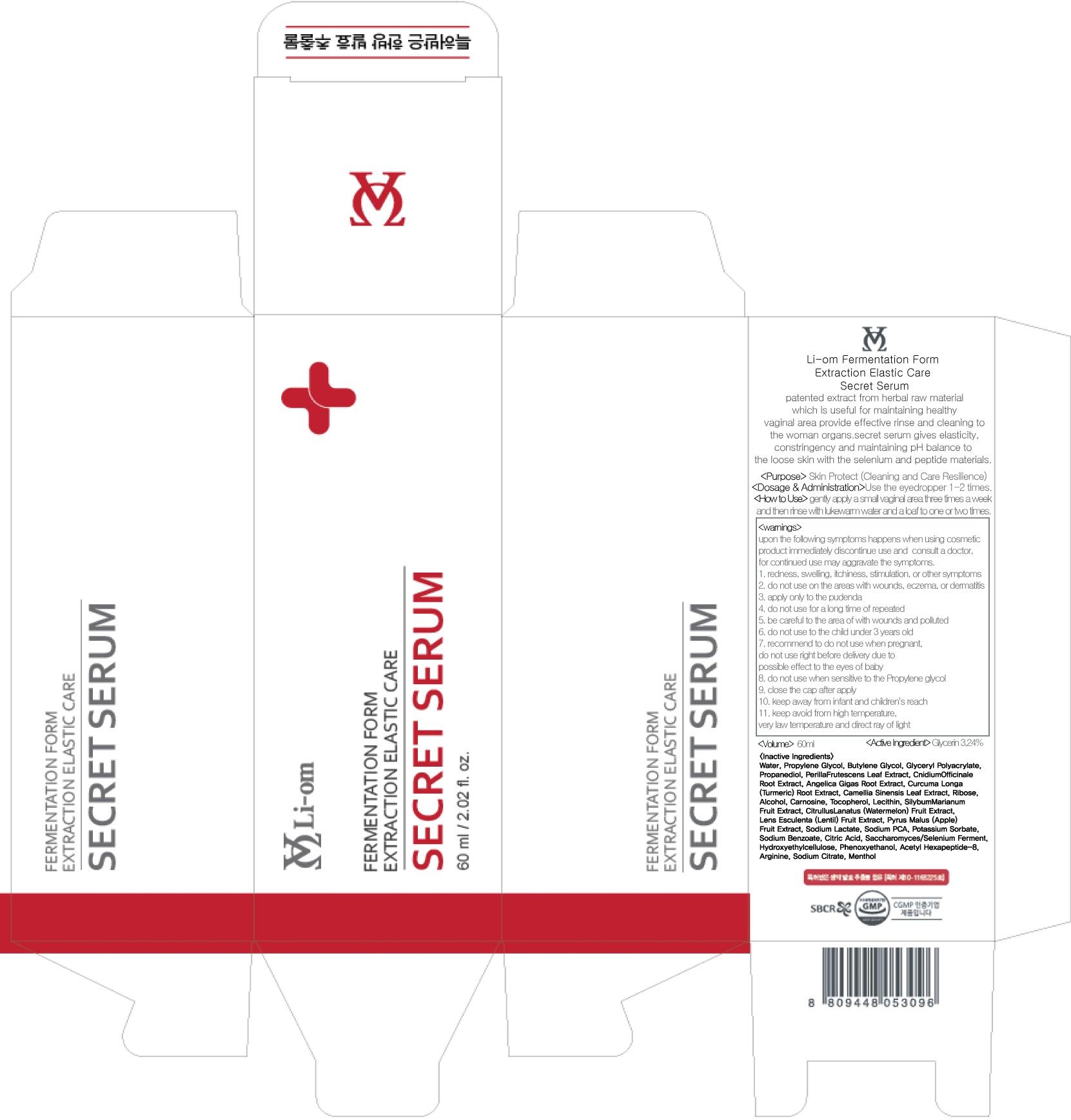 DRUG LABEL: Li om FERMENTATION FORM ELASTIC CARE SECRET SERUM
NDC: 70224-010 | Form: solution
Manufacturer: KOREAMEDICOS
Category: otc | Type: HUMAN OTC DRUG LABEL
Date: 20151112

ACTIVE INGREDIENTS: Glycerin 1.94 mg/60 mL
INACTIVE INGREDIENTS: Water; Propylene Glycol

ACTIVE INGREDIENT

Active Ingredient: Glycerin 3.24%

INACTIVE INGREDIENT

Inactive Ingredients: Water, Propylene Glycol, Butylene Glycol, Glyceryl Polyacrylate, Propanediol, PerillaFrutescens Leaf Extract, CnidiumOfficinale Root Extract, Angelica Gigas Root Extract, Curcuma Longa (Turmeric) Root Extract, Camellia Sinensis Leaf Extract, Ribose, Alcohol, Carnosine, Tocopherol, Lecithin, SilybumMarianum Fruit Extract, CitrullusLanatus (Watermelon) Fruit Extract, Lens Esculenta (Lentil) Fruit Extract, Pyrus Malus (Apple) Fruit Extract, Sodium Lactate, Sodium PCA, Potassium Sorbate, Sodium Benzoate, Citric Acid, Saccharomyces/Selenium Ferment, Hydroxyethylcellulose, Phenoxyethanol, Acetyl Hexapeptide-8, Arginine, Sodium Citrate, Menthol

PURPOSE

Purpose: Skin Protect (Cleaning and Care Resilience)

WARNINGS

Warnings upon the following symptoms happens when using cosmetic product immediately discontinue use and consult a doctor, for continued use may aggravate the symptoms. 1. redness, swelling, itchiness, stimulation, or other symptoms 2. do not use on the areas with wounds, eczema, or dermatitis 3. apply only to the pudenda 4. do not use for a long time of repeated 5. be careful to the area of with wounds and polluted 6. do not use to the child under 3 years old 7. recommend to do not use when pregnant, do not use right before delivery due to possible effect to the eyes of baby 8. do not use when sensitive to the Propylene glycol 9. close the cap after apply 10. keep away from infant and children's reach 11. keep avoid from high temperature, very law temperature and direct ray of light

KEEP OUT OF REACH OF CHILDREN

keep away from infant and children's reach

How to Use: Gently apply a small vaginal area three times a week and then rinse with lukewarm water and a loaf to one or two times.

DOSAGE & ADMINISTRATION

Dosage & Administration: Use the eyedropper 1-2 times.